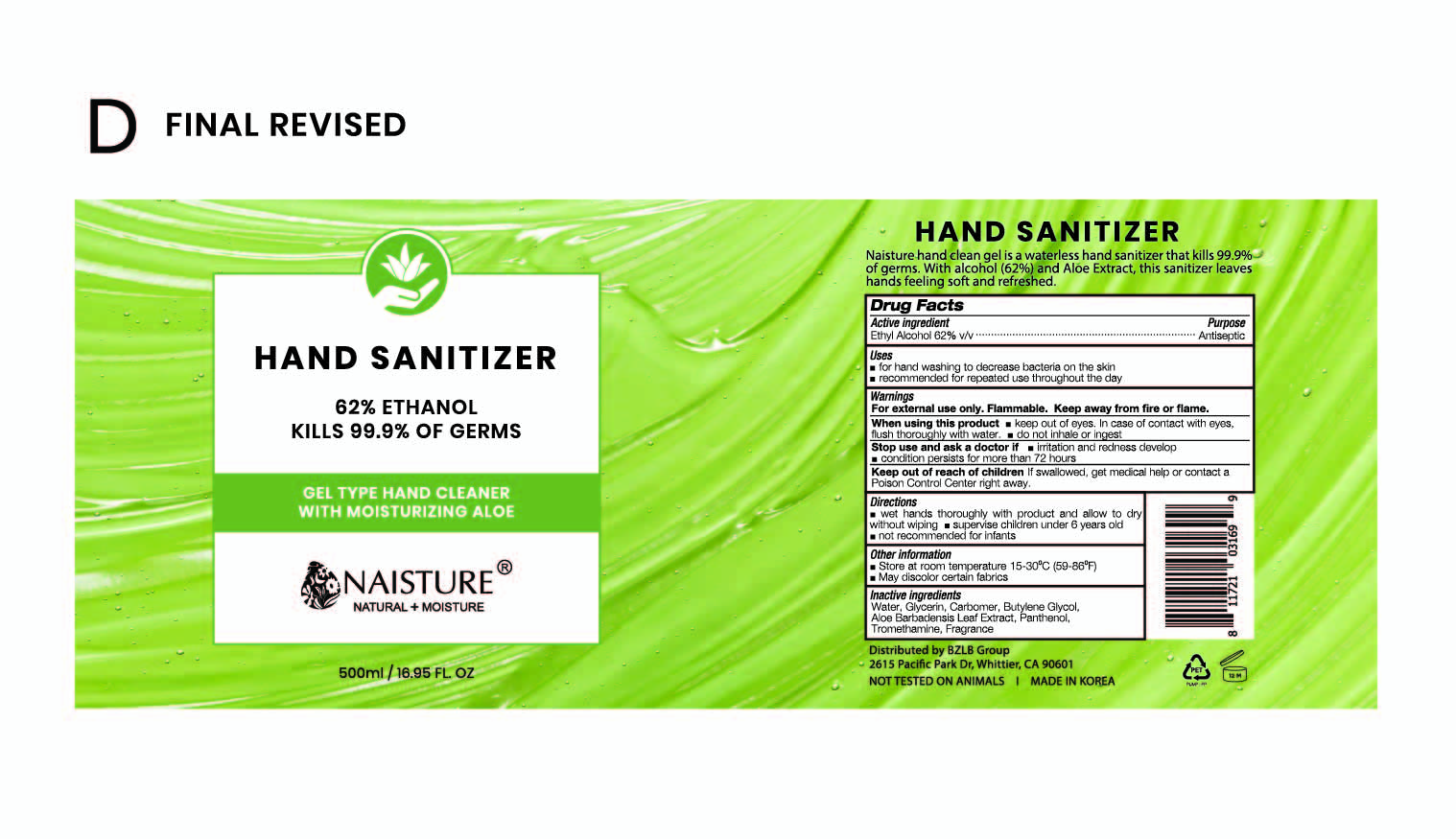 DRUG LABEL: Naisture Hand Sanitizer
NDC: 75024-500 | Form: GEL
Manufacturer: YOON JI CORPORATION CO.,LTD
Category: otc | Type: HUMAN OTC DRUG LABEL
Date: 20200424

ACTIVE INGREDIENTS: ALCOHOL 310 mL/500 mL
INACTIVE INGREDIENTS: ALOE VERA LEAF; GLYCERIN; BUTYLENE GLYCOL; CARBOMER HOMOPOLYMER, UNSPECIFIED TYPE; WATER; PANTHENOL; TROMETHAMINE

(UPDATE) Naisture Hand Sanitizer 500 ml : 75024-500-01